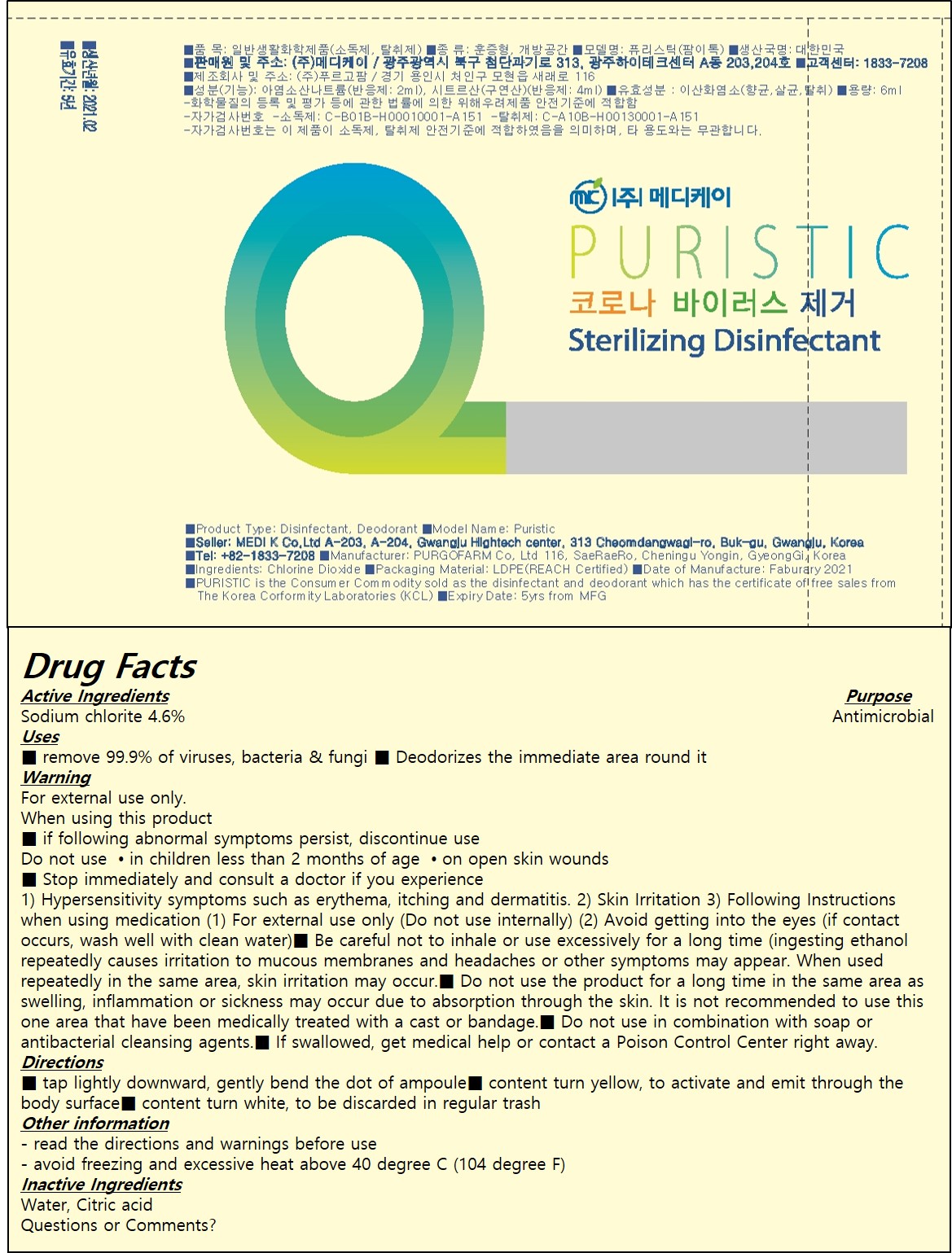 DRUG LABEL: PURISTIC
NDC: 82422-001 | Form: LIQUID
Manufacturer: MEDI K Co., Ltd.
Category: otc | Type: HUMAN OTC DRUG LABEL
Date: 20211126

ACTIVE INGREDIENTS: SODIUM CHLORITE 4.6 g/100 mL
INACTIVE INGREDIENTS: WATER; CITRIC ACID MONOHYDRATE

82422-001 PURISTIC

Active Ingredients

Sodium chlorite 4.6%

Purpose

Disinfecting Agent

Uses

■ remove 99.9% of viruses, bacteria & fungi
■ Deodorizes the immediate area round it

Warning

For external use only

■ If swallowed, get medical help or contact a Poison Control Center right away.

When using this product

■ if following abnormal symptoms persist, discontinue use

Do not use

- in children less than 2 months of age
- on open skin wounds

■ Do not use the product for a long time in the same area as swelling, inflammation or sickness
may occur due to absorption through the skin.
It is not recommended to use this one area that have been medically treated with a cast or
bandage.
■ Do not use in combination with soap or antibacterial cleansing agents.

ASK DOCTOR

■ Stop immediately and consult a doctor if you experience
1) Hypersensitivity symptoms such as erythema, itching and dermatitis.
2) Skin Irritation
3) Following Instructions when using medication
(1) For external use only (Do not use internally)
(2) Avoid getting into the eyes (if contact occurs, wash well with clean water)
■ Be careful not to inhale or use excessively for a long time (ingesting ethanol repeatedly causes irritation to mucous membranes and headaches or other symptoms may appear. When used repeatedly in the same area, skin irritation may occur.
■ Do not use the product for a long time in the same area as swelling, inflammation or sickness may occur due to absorption through the skin.

It is not recommended to use this one area that have been medically treated with a cast or
bandage.

- in children less than 2 months of age

Directions

■ tap lightly downward, gently bend the dot of ampoule
■ content turn yellow, to activate and emit through the body surface
■ content turn white, to be discarded in regular trash

Other information

- read the directions and warnings before use
- avoid freezing and excessive heat above 40 degree C (104 degree F)

Inactive Ingredients

Water, Citric acid